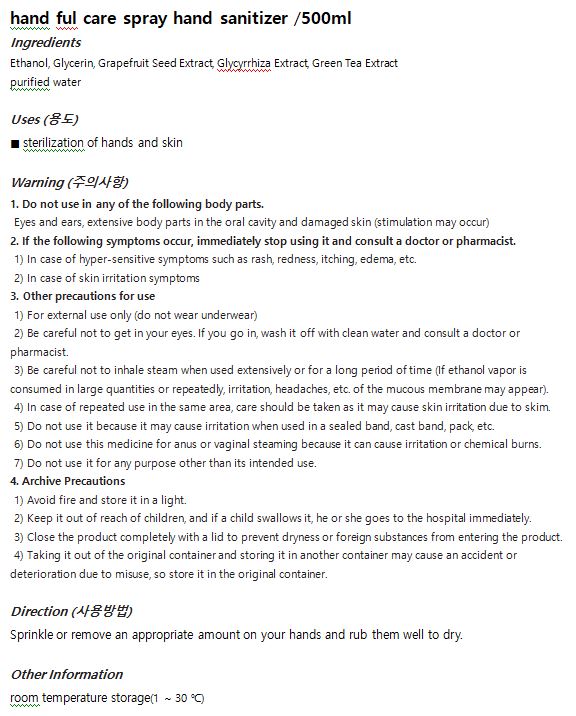 DRUG LABEL: hand ful care sprayhand sanitizer
NDC: 72139-0004 | Form: LIQUID
Manufacturer: SANDULBADA LIFE PHARM
Category: otc | Type: HUMAN OTC DRUG LABEL
Date: 20200909

ACTIVE INGREDIENTS: ALCOHOL 62 g/100 mL
INACTIVE INGREDIENTS: GREEN TEA LEAF; GRAPEFRUIT SEED OIL; WATER; LICORICE; GLYCERIN

Drug Facts

ACTIVE INGREDIENT

ethanol

PURPOSE

■ sterilization of hands and skin

KEEP OUT OF REACH OF THE CHILDREN

WARNINGS

■ Flammable. Keep away from fire or flame.

■ For external use only.

■ Do not use in eyes.

■ lf swallowed, get medical help promptly.

■ Stop use, ask doctor lf irritation occurs.

■ Keep out of reach of children.

DOSAGE AND ADMINISTRATION

for external use only

INACTIVE INGREDIENT

Ethanol, Glycerin, Grapefruit Seed Extract, Glycyrrhiza Extract, Green Tea Extract

INDICATIONS AND USAGE

wet hands thoroughly with product and allow to dry without wiping

for children under 6, use only under adult supervision

not recommended for infants